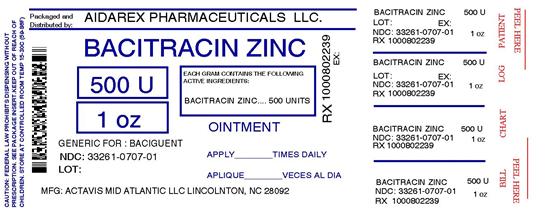 DRUG LABEL: Bacitracin Zinc
NDC: 33261-707 | Form: OINTMENT
Manufacturer: Aidarex Pharmaceuticals LLC
Category: otc | Type: HUMAN OTC DRUG LABEL
Date: 20120910

ACTIVE INGREDIENTS: BACITRACIN ZINC 500 [USP'U]/1 g
INACTIVE INGREDIENTS: PETROLATUM

Bacitracin Zinc Ointment, USP

ACTIVE INGREDIENT

(in each gram)

Bacitracin zinc, USP 500 units

PURPOSE

First aid antibiotic

USES

Helps prevent infection in

- minor cuts
- scrapes
- burns

WARNINGS

For external use only

Allergy alert:

- do not use if allergic to any of the ingredients

DO NOT USE

- in the eyes
- over large areas of the body

ASK A DOCTOR BEFORE USE IF YOU HAVE

- deep or puncture wounds
- animal bites
- serious burns

WHEN USING THIS PRODUCT

- do not use longer than 1 week unless directed by a doctor

STOP USE AND ASK A DOCTOR IF

- condition persists or gets worse
- a rash or other allergic reaction develops

KEEP OUT OF REACH OF CHILDREN

If swallowed, get medical help or contact a Poison Control Center right away.

DIRECTIONS

- clean affected area
- apply a small amount (equal to the surface area of the tip of a finger) on the area 1 to 3 times daily
- may be covered with a sterile bandage

OTHER INFORMATION

- Store at room temperature 59°-77°F (15°-25°C).

INACTIVE INGREDIENT

White petrolatum

QUESTIONS?

1-800-432-8534 between 9 am and 4 pm EST, Monday–Friday.

PACKAGE LABEL.PRINCIPAL DISPLAY PANEL

Repackaged By:
Aidarex Pharmaceuticals, LLC
Corona, CA 92880

NDC 33261-707-01

Bacitracin Zinc Ointment, USP

First Aid Antibiotic Ointment

Net WT 1 OZ (28 g)

11051210E1 VC110188

Image Label